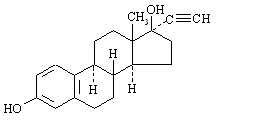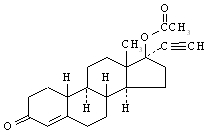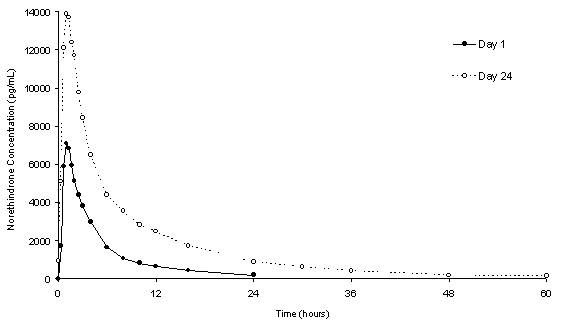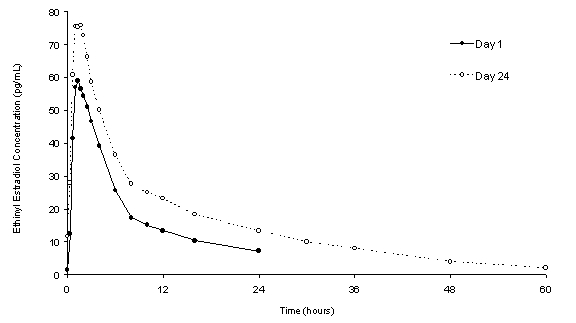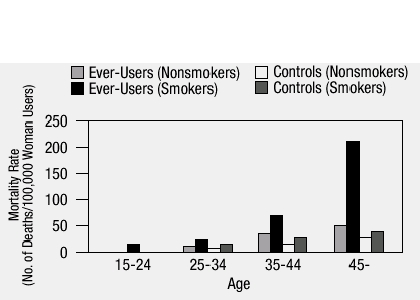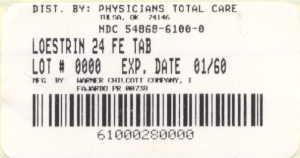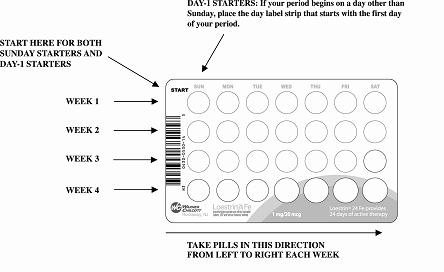 DRUG LABEL: Loestrin 24 Fe
NDC: 54868-6100 | Form: KIT | Route: ORAL
Manufacturer: Physicians Total Care, Inc.
Category: prescription | Type: HUMAN PRESCRIPTION DRUG LABEL
Date: 20100209

ACTIVE INGREDIENTS: NORETHINDRONE ACETATE 1 mg/1 1; ETHINYL ESTRADIOL 20 ug/1 1
INACTIVE INGREDIENTS: ACACIA; LACTOSE; MAGNESIUM STEARATE; STARCH, CORN; TALC; SUCROSE; FERROUS FUMARATE 75 mg/1 1; CELLULOSE, MICROCRYSTALLINE; MAGNESIUM STEARATE; POVIDONE; SODIUM STARCH GLYCOLATE TYPE A POTATO; SUCROSE

(norethindrone acetate and ethinyl estradiol tablets, USP and ferrous fumarate tablets)
Ferrous fumarate tablets are not USP for dissolution and assay.

Rx Only

Patients should be counseled that this product does not protect against HIV infection (AIDS) and other sexually transmitted diseases.

BOXED WARNING

Cigarette smoking increases the risk of serious cardiovascular side effects from oral contraceptive use. This risk increases with age and with the extent of smoking (in epidemiologic studies, 15 or more cigarettes per day was associated with a significantly increased risk) and is quite marked in women over 35 years of age. Women who use oral contraceptives should be strongly advised not to smoke.

DESCRIPTION

Loestrin® 24 Fe provides a dosage regimen consisting of 24 white progestogen-estrogen contraceptive tablets and 4 brown ferrous fumarate (placebo) tablets.

Each white tablet contains 1 mg norethindrone acetate and 20 mcg ethinyl estradiol.
Each white tablet also contains the following inactive ingredients: acacia, lactose, magnesium stearate, starch, confectioner’s sugar, and talc.

Each brown tablet contains ferrous fumarate, microcrystalline cellulose, magnesium stearate, povidone, sodium starch glycolate, and compressible sugar. The ferrous fumarate tablets do not serve any therapeutic purpose.

The structural formulas for the active hormones are:

Ethinyl Estradiol [19-Norpregna-1,3,5(10)-trien-20-yne-3,17-diol, (17α)-]

Norethindrone Acetate [19-Norpregn-4-en-20-yn-3-one, 17-(acetyloxy)-, (17α)-]

CLINICAL PHARMACOLOGY

Combination oral contraceptives act by suppression of gonadotropins. Although the primary mechanism of this action is inhibition of ovulation, other alterations include changes in the cervical mucus (which increase the difficulty of sperm entry into the uterus) and the endometrium (which reduce the likelihood of implantation).

PHARMACOKINETICS

Absorption

Norethindrone acetate appears to be completely and rapidly deacetylated to norethindrone after oral administration, because the disposition of norethindrone acetate is indistinguishable from that of orally administered norethindrone. Norethindrone acetate and ethinyl estradiol are rapidly absorbed from Loestrin 24 Fe tablets, with maximum plasma concentrations of norethindrone and ethinyl estradiol occurring 1 to 4 hours postdose. Both are subject to first-pass metabolism after oral dosing, resulting in an absolute bioavailability of approximately 64% for norethindrone and 43% for ethinyl estradiol.

The plasma norethindrone and ethinyl estradiol pharmacokinetics following single- and multiple-dose administrations of Loestrin 24 Fe tablets in 17 healthy female volunteers are provided in Figures 1 and 2, and Table 1.

Following multiple-dose administration of Loestrin 24 Fe tablets, mean maximum concentrations of norethindrone and ethinyl estradiol were increased by 95% and 27%, respectively, as compared to single-dose administration. Mean norethindrone and ethinyl estradiol exposures (AUC values) were increased by 164% and 51% respectively, as compared to single-dose administration of Loestrin 24 Fe tablets.

Steady-state with respect to norethindrone was reached by Day 17 and steady-state with respect to ethinyl estradiol was reached by Day 13.

Mean SHBG concentrations were increased by 150% from baseline (57.5 nmol/L) to 144 nmol/L at steady-state.

Figure 1. Mean Plasma Norethindrone Concentration-Time Profiles Following Single- and Multiple-Dose Oral Administration of Loestrin 24 Fe Tablets to Healthy Female Volunteers under Fasting Condition (n = 17)

Figure 2. Mean Plasma Ethinyl Estradiol Concentration-Time Profiles Following Single- and Multiple-Dose Oral Administration of Loestrin 24 Fe Tablets to Healthy Female Volunteers under Fasting Condition (n = 17)

Table 1. Summary of Norethindrone (NE) and Ethinyl Estradiol (EE) Pharmacokinetics Following Single- and Multiple-Dose Oral Administration of Loestrin 24 Fe Tablets to Healthy Female Volunteers under Fasting Condition (n = 17)
 |  | Arithmetic | Mean* (%CV) | by Pharmacokinetic | Parameter
Regimen | Analyte | Cmax; (pg/mL) | tmax; (hr) | AUC(0-24); (pg/mL•h) | Cmin; (pg/mL) | t½; (hr) | Cavg; (pg/mL)
 | NE | 8420 (31) | 1.0 (0.7-4.0) | 33390 (40) | -- | -- | --
Day 1 (Single Dose) | EE | 64.5 (27) | 1.3 (0.7-4.0) | 465.4 (26) | -- | -- | --
 | SHBG | -- | -- | -- | 57.5 (37)† | -- | --
 | NE | 16400 (26) | 1.3 (0.7-4.0) | 88160 (30) | 880 (51) | 8.4 | 3670 (30)
Day 24 (Multiple Dose) | EE | 81.9 (24) | 1.7 (1.0-2.0) | 701.3 (28) | 11.4 (43) | 14.5 | 29.2 (28)
 | SHBG | -- | -- | -- | 144 (24) | -- | --

Cmax = Maximum plasma concentration; tmax = Time of Cmax ; Cmin = minimum plasma concentration at steady-state ; AUC(0-24) = Area under plasma concentration versus time curve from 0 to 24 hours ; t½ = Apparent first-order terminal elimination half-life ; Cavg = Average plasma concentration = AUC(0–24)/24 %CV = Coefficient of Variation (%); SHBG = Sex Hormone Binding Globulin (nmol/L)
* The harmonic mean (0.693/mean apparent elimination rate constant) is reported for t½, and the median (range) is reported for tmax.
† The SHBG concentration reported here is the pre-dose concentration.

Effect of Food: Loestrin 24 Fe tablets may be administered without regard to meals. A single-dose administration of Loestrin 24 Fe tablet with food decreased the maximum concentration of norethindrone by 11% and increased the extent of absorption by 27% and decreased the maximum concentration of ethinyl estradiol by 30% but not the extent of absorption.

Distribution

Volume of distribution of norethindrone and ethinyl estradiol ranges from 2 to 4 L/kg. Plasma protein binding of both steroids is extensive (>95%); norethindrone binds to both albumin and SHBG, whereas ethinyl estradiol binds only to albumin. Although ethinyl estradiol does not bind to SHBG, it induces SHBG synthesis.

Metabolism

Norethindrone undergoes extensive biotransformation, primarily via reduction, followed by sulfate and glucuronide conjugation. The majority of metabolites in the circulation are sulfates, with glucuronides accounting for most of the urinary metabolites.

Ethinyl estradiol is also extensively metabolized, both by oxidation and by conjugation with sulfate and glucuronide. Sulfates are the major circulating conjugates of ethinyl estradiol and glucuronides predominate in urine. The primary oxidative metabolite is 2-hydroxy ethinyl estradiol, formed by the CYP3A4 isoform of cytochrome P450. Part of the first-pass metabolism of ethinyl estradiol is believed to occur in gastrointestinal mucosa. Ethinyl estradiol may undergo enterohepatic circulation.

Excretion

Norethindrone and ethinyl estradiol are excreted in both urine and feces, primarily as metabolites. Plasma clearance values for norethindrone and ethinyl estradiol are similar (approximately 0.4 L/hr/kg). Steady-state elimination half-lives of norethindrone and ethinyl estradiol following administration of Loestrin 24 Fe tablets are approximately 8 hours and 14 hours, respectively.

Special Populations

Race. The effect of race on the disposition of norethindrone and ethinyl estradiol after Loestrin 24 Fe administration has not been evaluated.

Renal Insufficiency. The effect of renal disease on the disposition of norethindrone and ethinyl estradiol after Loestrin 24 Fe administration has not been evaluated. In premenopausal women with chronic renal failure undergoing peritoneal dialysis who received multiple doses of an oral contraceptive containing ethinyl estradiol and norethindrone, plasma ethinyl estradiol concentrations were higher and norethindrone concentrations were unchanged compared to concentrations in premenopausal women with normal renal function.

Hepatic Insufficiency. The effect of hepatic disease on the disposition of norethindrone and ethinyl estradiol after Loestrin 24 Fe administration has not been evaluated. However, ethinyl estradiol and norethindrone may be poorly metabolized in patients with impaired liver function.

Drug-Drug Interactions

See PRECAUTIONS section— DRUG INTERACTIONS

INDICATIONS AND USAGE

Loestrin 24 Fe is indicated for the prevention of pregnancy in women who elect to use oral contraceptives as a method of contraception.

Oral contraceptives are highly effective. Table 2 lists the typical unplanned pregnancy rates for users of combination oral contraceptives and other methods of contraception. The efficacy of these contraceptive methods, except sterilization, the IUD, and the Norplant® system, depends upon the reliability with which they are used. Correct and consistent use of methods can result in lower failure rates.

TABLE 2 Percentage of women experiencing an unintended pregnancy during the first year of typical use and the first year of perfect use of contraception and the percentage continuing use at the end of the first year. United States.
 | % of Women Unintended the First Year | Experiencing an Pregnancy with of Use | % of Women Continuing Use at One Year*
Method (1) | Typical Use† (2) | Perfect Use‡ (3) | (4)
Chance§ | 85 | 85
Spermicides¶ | 26 | 6 | 40
Periodic abstinence | 25 |  | 63
Calendar |  | 9
Ovulation Method |  | 3
Sympto-thermal# |  | 2
Post-Ovulation |  | 1
CapÞ
Parous Women | 40 | 26 | 42
Nulliparous Women | 20 | 9 | 56
Sponge
Parous Women | 40 | 20 | 42
Nulliparous Women | 20 | 9 | 56
DiaphragmÞ | 20 | 6 | 56
Withdrawal | 19 | 4
Condomß
Female (reality) | 21 | 5 | 56
Male | 14 | 3 | 61
Pill | 5 |  | 71
Progestin only |  | 0.5
Combined |  | 0.1
IUD
Progesterone T | 2.0 | 1.5 | 81
Copper T 380A | 0.8 | 0.6 | 78
LNg 20 | 0.1 | 0.1 | 81
Depo-Provera® | 0.3 | 0.3 | 70
Norplant® and Norplant® 2 | 0.05 | 0.05 | 88
Female Sterilization | 0.5 | 0.5 | 100
Male Sterilization | 0.15 | 0.10 | 100

Emergency Contraceptive Pills: Treatment initiated within 72 hours after unprotected intercourse
reduces risk of pregnancy by at least 75% à
Lactational Amenorrhea Method: LAM is a highly effective, temporary method of contraception è
Source: Trussell J, Stewart F, Contraceptive Efficacy. In Hatcher RA, Trussell J, Stewart F, Cates W,
Stewart GK, Kowal D, Guest F, Contraceptive Technology: Seventeenth Revised Edition.
New York, NY: Irvington Publishers, 1998.
* Among couples attempting to avoid pregnancy, the percentage who continue to use a method for one year
† Among typical couples who initiate use of a method (not necessarily for the first time), the percentage who experience an accidental pregnancy during the first year if they do not stop use for any other reason
‡ Among couples who initiate use of a method (not necessarily for the first time) and who use it perfectly (both consistently
and correctly), the percentage who experience an accidental pregnancy during the first year if they do not stop use for any other reason
§ The percentage of women becoming pregnant noted in columns (2) and (3) are based on data from populations where contraception is not used and from women who cease using contraception in order to become pregnant. Among such
populations, about 89% became pregnant in one year. This estimate was lowered slightly (to 85%) to represent the percentage
that would become pregnant within one year among women now relying on reversible methods of contraception if they abandon contraception altogether
¶ Foams, creams, gels, vaginal suppositories and vaginal film
# Cervical mucous (ovulation) method supplemented by calendar in the preovulatory and basal body temperature in the postovulatory phases
Þ With spermicidal cream or jelly
ß Without spermicides
à The treatment schedule is one dose within 72 hours after unprotected intercourse and a second dose 12 hours after the first
dose. The Food and Drug Administration has declared the following brands of oral contraceptives to be safe and effective for emergency contraception: Ovral® (1 dose is 2 white pills), Alesse® (1 dose is 5 pink pills), Nordette® or Levlen® (1 dose is 2 light orange pills), Lo/Ovral® (1 dose is 4 white pills), Triphasil® or Tri-Levlen® (1 dose is 4 yellow pills)
è
However, to maintain effective protection against pregnancy, another method of contraception must be used as soon as menstruation resumes, the frequency or duration of breastfeeds is reduced, bottle feeds are introduced or the baby reaches six months of age
Clinical Studies

In a clinical study, 743 women, 18 to 45 years of age, were treated with Loestrin 24 Fe for up to six 28-day cycles providing a total of 3,823 treatment-cycles of exposure. A total of 583 women completed 6 cycles of treatment. There were a total of 5 on-treatment pregnancies in 3,565 treatment cycles during which no backup contraception was used. The Pearl Index for Loestrin 24 Fe was 1.82.

CONTRAINDICATIONS

Oral contraceptives should not be used in women who currently have the following conditions:

- Thrombophlebitis or thromboembolic disorders
- A past history of deep vein thrombophlebitis or thromboembolic disorders
- Cerebrovascular or coronary artery disease (current or history)
- Valvular heart disease with thrombogenic complications
- Severe hypertension
- Diabetes with vascular involvement
- Headaches with focal neurological symptoms
- Major surgery with prolonged immobilization
- Known or suspected carcinoma of the breast or personal history of breast cancer
- Carcinoma of the endometrium or other known or suspected estrogen-dependent neoplasia
- Undiagnosed abnormal genital bleeding
- Cholestatic jaundice of pregnancy or jaundice with prior pill use
- Hepatic adenomas or carcinomas, or active liver disease
- Known or suspected pregnancy
- Hypersensitivity to any component of this product

WARNINGS

Cigarette smoking increases the risk of serious cardiovascular side effects from oral contraceptive use. This risk increases with age and with the extent of smoking (in epidemiologic studies, 15 or more cigarettes per day was associated with a significantly increased risk) and is quite marked in women over 35 years of age. Women who use oral contraceptives should be strongly advised not to smoke.

The use of oral contraceptives is associated with increased risk of several serious conditions including venous and arterial thrombotic and thromboembolic events (such as myocardial infarction, thromboembolism, and stroke), hepatic neoplasia, gallbladder disease, and hypertension, although the risk of serious morbidity or mortality is very small in healthy women without underlying risk factors. The risk of morbidity and mortality increases significantly in the presence of other underlying risk factors such as certain inherited thrombophilias, hypertension, hyperlipidemias, obesity and diabetes.

Practitioners prescribing oral contraceptives should be familiar with the following information relating to these risks. The information contained in this package insert is principally based on studies carried out in patients who used oral contraceptives with higher formulations of estrogens and progestogens than those in common use today. The effect of long-term use of the oral contraceptives with lower formulations of both estrogens and progestogens remains to be determined.

Throughout this labeling, epidemiological studies reported are of two types: retrospective or case control studies and prospective or cohort studies. Case control studies provide a measure of the relative risk of a disease, namely, a ratio of the incidence of a disease among oral contraceptive users to that among nonusers. The relative risk does not provide information on the actual clinical occurrence of a disease. Cohort studies provide a measure of attributable risk, which is the difference in the incidence of disease between oral contraceptive users and nonusers. The attributable risk does provide information about the actual occurrence of a disease in the population. For further information, the reader is referred to a text on epidemiological methods.

1. THROMBOEMBOLIC DISORDERS AND OTHER VASCULAR PROBLEMSa. Myocardial Infarction

An increased risk of myocardial infarction has been attributed to oral contraceptive use. This risk is primarily in smokers or women with other underlying risk factors for coronary artery disease such as hypertension, hypercholesterolemia, morbid obesity, and diabetes. The relative risk of heart attack for current oral contraceptive users has been estimated to be two to six. The risk is very low under the age of 30.

Smoking in combination with oral contraceptive use has been shown to contribute substantially to the incidence of myocardial infarctions in women in their mid-thirties or older, with smoking accounting for the majority of excess cases. Mortality rates associated with circulatory disease have been shown to increase substantially in smokers over the age of 35 and nonsmokers over the age of 40 (Figure 3) among women who use oral contraceptives.

FIGURE 3. CIRCULATORY DISEASE MORTALITY RATES FOR 100,000 WOMEN-YEARS BY AGE, SMOKING STATUS AND ORAL CONTRACEPTIVE USE

Layde PM, Beral V. Lancet 1981;1:541-546.

Oral contraceptives may compound the effects of well-known risk factors, such as hypertension, diabetes, hyperlipidemias, age, and obesity. In particular, some progestogens are known to decrease HDL cholesterol and cause glucose intolerance, while estrogens may create a state of hyperinsulinism. Oral contraceptives have been shown to increase blood pressure among users (see section 9 in WARNINGS). Such increases in risk factors have been associated with an increased risk of heart disease and the risk increases with the number of risk factors present. Oral contraceptives must be used with caution in women with cardiovascular disease risk factors.

b. Thromboembolism

An increased risk of thromboembolic and thrombotic disease associated with the use of oral contraceptives is well established. Case control studies have found the relative risk of users compared to non-users to be 3 for the first episode of superficial venous thrombosis, 4 to 11 for deep vein thrombosis or pulmonary embolism, and 1.5 to 6 for women with predisposing conditions for venous thromboembolic disease. Cohort studies have shown the relative risk to be somewhat lower, about 3 for new cases and about 4.5 for new cases requiring hospitalization. The risk of thromboembolic disease due to oral contraceptives is not related to length of use and disappears after pill use is stopped.

A two- to four-fold increase in relative risk of postoperative thromboembolic complications has been reported with the use of oral contraceptives. The relative risk of venous thrombosis in women who have predisposing conditions is twice that of women without such medical conditions. If feasible, oral contraceptives should be discontinued at least four weeks prior to and for two weeks after elective surgery of a type associated with an increase in risk of thromboembolism and during and following prolonged immobilization. Since the immediate postpartum period is also associated with an increased risk of thromboembolism, oral contraceptives should be started no earlier than four to six weeks after delivery in women who elect not to breastfeed.

c. Cerebrovascular diseases

Oral contraceptives have been shown to increase both the relative and attributable risk of cerebrovascular events (thrombotic and hemorrhagic strokes) although, in general, the risk is greatest among older (>35 years), hypertensive women who also smoke. Hypertension was found to be a risk factor for both users and nonusers, for both types of strokes, while smoking interacted to increase the risk for hemorrhagic strokes.

In a large study, the relative risk of thrombotic strokes has been shown to range from 3 for normotensive users to 14 for users with severe hypertension. The relative risk of hemorrhagic stroke is reported to be 1.2 for nonsmokers who used oral contraceptives, 2.6 for smokers who did not use oral contraceptives, 7.6 for smokers who used oral contraceptives, 1.8 for normotensive users and 25.7 for users with severe hypertension. The attributable risk is also greater in older women. Oral contraceptives also increase the risk for stroke in women with other underlying risk factors such as certain inherited or acquired thrombophilias, hyperlipidemias, and obesity. Women with migraine (particularly migraine with aura) who take combination oral contraceptives may be at an increased risk of stroke.

d. Dose-related risk of vascular disease from oral contraceptives

A positive association has been observed between the amount of estrogen and progestogen in oral contraceptives and the risk of vascular disease. A decline in serum high-density lipoproteins (HDL) has been reported with many progestational agents. A decline in serum high-density lipoproteins has been associated with an increased incidence of ischemic heart disease. Because estrogens increase HDL cholesterol, the net effect of an oral contraceptive depends on a balance achieved between doses of estrogen and progestogen and the nature and absolute amount of progestogens used in the contraceptive. The amount of both hormones should be considered in the choice of an oral contraceptive.

Minimizing exposure to estrogen and progestogen is in keeping with good principles of therapeutics. For any particular estrogen/progestogen combination, the dosage regimen prescribed should be one which contains the least amount of estrogen and progestogen that is compatible with a low failure rate and the needs of the individual patient. New acceptors of oral contraceptive agents should be started on preparations containing the lowest estrogen content which is judged appropriate for the individual patient.

e. Persistence of risk of vascular disease

There are two studies which have shown persistence of risk of vascular disease for ever-users of oral contraceptives. In a study in the United States, the risk of developing myocardial infarction after discontinuing oral contraceptives persisted for at least 9 years for women 40 to 49 years old who had used oral contraceptives for five or more years but this increased risk was not demonstrated in other age groups. In another study in Great Britain, the risk of developing cerebrovascular disease persisted for at least 6 years after discontinuation of oral contraceptives, although excess risk was very small. However, both studies were performed with oral contraceptive formulations containing 50 micrograms or higher of estrogens.

2. ESTIMATES OF MORTALITY FROM CONTRACEPTIVE USE

One study gathered data from a variety of sources which have estimated the mortality rate associated with different methods of contraception at different ages (Table 3).

TABLE 3 ANNUAL NUMBER OF BIRTH-RELATED OR METHOD-RELATED DEATHS ASSOCIATED WITH CONTROL OF FERTILITY PER 100,000 NONSTERILE WOMEN, BY FERTILITY CONTROL METHOD ACCORDING TO AGE
 |  |  | AGE
Method of control and outcome | 15-19 | 20-24 | 25-29 | 30-34 | 35-39 | 40-44
No fertility control methods* | 7.0 | 7.4 | 9.1 | 14.8 | 25.7 | 28.2
Oral contraceptives nonsmoker† | 0.3 | 0.5 | 0.9 | 1.9 | 13.8 | 31.6
Oral contraceptives smoker† | 2.2 | 3.4 | 6.6 | 13.5 | 51.1 | 117.2
IUD† | 0.8 | 0.8 | 1.0 | 1.0 | 1.4 | 1.4
Condom* | 1.1 | 1.6 | 0.7 | 0.2 | 0.3 | 0.4
Diaphragm/spermicide* | 1.9 | 1.2 | 1.2 | 1.3 | 2.2 | 2.8
Periodic abstinence* | 2.5 | 1.6 | 1.6 | 1.7 | 2.9 | 3.6

Ory HW. Family Planning Perspectives 1983; 15:57-63.
* Deaths are birth related
† Deaths are method related

These estimates include the combined risk of death associated with contraceptive methods plus the risk attributable to pregnancy in the event of method failure. Each method of contraception has its specific benefits and risk. The study concluded that with the exception of oral contraceptive users 35 and older who smoke and 40 and older who do not smoke, mortality associated with all methods of birth control is low and below that associated with childbirth.

The observation of a possible increase in risk of mortality with age for oral contraceptive users is based on data gathered in the 1970s but not reported until 1983. However, current clinical practice involves the use of lower estrogen dose formulations combined with careful restriction of oral contraceptive use to women who do not have the various risk factors listed in this labeling.

Because of these changes in practice and, also, because of some limited new data which suggest that the risk of cardiovascular disease with the use of oral contraceptives may now be less than previously observed, the Fertility and Maternal Health Drugs Advisory Committee was asked to review the topic in 1989. The Committee concluded that although cardiovascular disease risk may be increased with oral contraceptive use after age 40 in healthy nonsmoking women (even with the newer low-dose formulations), there are greater potential health risks associated with pregnancy in older women and with the alternative surgical and medical procedures which may be necessary if such women do not have access to effective and acceptable means of contraception.

Therefore, the Committee recommended that the benefits of oral contraceptive use by healthy nonsmoking women over 40 may outweigh the possible risks. Of course, older women, as all women who take oral contraceptives, should take the lowest possible dose formulation that is effective and meets the individual patient needs.

3. CARCINOMA OF THE REPRODUCTIVE ORGANS AND BREASTS

Numerous epidemiological studies have been performed on the incidence of breast, endometrial, ovarian, and cervical cancer in women using oral contraceptives. Although the risk of breast cancer may be slightly increased among current users of oral contraceptives (RR = 1.24), this excess risk decreases over time after oral contraceptive discontinuation and by 10 years after cessation the increased risk disappears. The risk does not increase with duration of use, and no relationships have been found with dose or type of steroid. The patterns of risk are also similar regardless of a woman's reproductive history or her family breast cancer history. The subgroup for whom risk has been found to be significantly elevated is women who first used oral contraceptives before age 20, but because breast cancer is so rare at these young ages, the number of cases attributable to this early oral contraceptive use is extremely small. Breast cancers diagnosed in current or previous oral contraceptive users tend to be less advanced clinically than in never-users. Women who currently have or have had breast cancer should not use oral contraceptives because breast cancer is a hormone-sensitive tumor.

Some studies suggest that oral contraceptive use has been associated with an increase in the risk of cervical intraepithelial neoplasia or invasive cervical cancer in some populations of women. However, there continues to be controversy about the extent to which such findings may be due to differences in sexual behavior and other factors.

In spite of many studies of the relationship between oral contraceptive use and breast cancer and cervical cancers, a cause-and-effect relationship has not been established.

4. HEPATIC NEOPLASIA

Benign hepatic adenomas are associated with oral contraceptive use, although their occurrence is rare in the United States. Indirect calculations have estimated the attributable risk to be in the range of 3.3 cases/100,000 for users, a risk that increases after four or more years of use. Rupture of hepatic adenomas may cause death through intra-abdominal hemorrhage.

Studies from Britain have shown an increased risk of developing hepatocellular carcinoma in long-term (>8 years) oral contraceptive users. However, these cancers are extremely rare in the U.S. and the attributable risk (the excess incidence) of liver cancers in oral contraceptive users approaches less than one per million users.

5. OCULAR LESIONS

There have been clinical case reports of retinal thrombosis associated with the use of oral contraceptives that may lead to partial or complete loss of vision. Oral contraceptives should be discontinued if there is unexplained partial or complete loss of vision; onset of proptosis or diplopia; papilledema; or retinal vascular lesions. Appropriate diagnostic and therapeutic measures should be undertaken immediately.

6. ORAL CONTRACEPTIVE USE BEFORE OR DURING EARLY PREGNANCY

Extensive epidemiological studies have revealed no increased risk of birth defects in women who have used oral contraceptives prior to pregnancy. Studies also do not suggest a teratogenic effect, particularly in so far as cardiac anomalies and limb reduction defects are concerned, when taken inadvertently during early pregnancy (see CONTRAINDICATIONS section).

The administration of oral contraceptives to induce withdrawal bleeding should not be used as a test for pregnancy. Oral contraceptives should not be used during pregnancy to treat threatened or habitual abortion.

It is recommended that for any patient who has missed two consecutive periods, pregnancy should be ruled out. If the patient has not adhered to the prescribed schedule, the possibility of pregnancy should be considered at the time of the first missed period. Oral contraceptive use should be discontinued if pregnancy is confirmed.

7. GALLBLADDER DISEASE

Earlier studies have reported an increased lifetime relative risk of gallbladder surgery in users of oral contraceptives and estrogens. More recent studies, however, have shown that the relative risk of developing gallbladder disease among oral contraceptive users may be minimal. The recent findings of minimal risk may be related to the use of oral contraceptive formulations containing lower hormonal doses of estrogens and progestogens.

8. CARBOHYDRATE AND LIPID METABOLIC EFFECTS

Oral contraceptives have been shown to cause glucose intolerance in a significant percentage of users. Oral contraceptives containing greater than 75 micrograms of estrogens cause hyperinsulinism, while lower doses of estrogen cause less glucose intolerance. Progestogens increase insulin secretion and create insulin resistance, this effect varying with different progestational agents. However, in the nondiabetic woman, oral contraceptives appear to have no effect on fasting blood glucose. Because of these demonstrated effects, prediabetic and diabetic women should be carefully observed while taking oral contraceptives.

A small proportion of women will have persistent hypertriglyceridemia while on the pill. As discussed earlier (see WARNINGS 1.a. and 1.d.), changes in serum triglycerides and lipoprotein levels have been reported in oral contraceptive users.

9. ELEVATED BLOOD PRESSURE

Women with significant hypertension should not be started on hormonal contraceptives. An increase in blood pressure has been reported in women taking oral contraceptives, and this increase is more likely in older oral contraceptive users and with continued use. Data from the Royal College of General Practitioners and subsequent randomized trials have shown that the incidence of hypertension increases with increasing concentrations of progestogens.

Women with a history of hypertension or hypertension-related diseases, or renal disease should be encouraged to use another method of contraception. If women elect to use oral contraceptives, they should be monitored closely and if significant elevation of blood pressure occurs, oral contraceptives should be discontinued (see CONTRAINDICATIONS section). For most women, elevated blood pressure will return to normal after stopping oral contraceptives, and there is no difference in the occurrence of hypertension among ever- and never-users.

10. HEADACHE

The onset or exacerbation of migraine or development of headache with a new pattern which is recurrent, persistent, or severe requires discontinuation of oral contraceptives and evaluation of the cause (see WARNINGS 1.c.).

11. BLEEDING IRREGULARITIES

Breakthrough bleeding and spotting are sometimes encountered in patients on oral contraceptives, especially during the first three months of use. If bleeding persists or recurs, nonhormonal causes should be considered and adequate diagnostic measures taken to rule out malignancy or pregnancy as in the case of any abnormal vaginal bleeding. If pathology has been excluded, time or a change to another formulation may solve the problem.

Absence of a withdrawal menses may also occur. In the event of amenorrhea for two cycles or more, pregnancy should be ruled out. In the clinical trial with Loestrin 24 Fe, 31-41% of the women using Loestrin 24 Fe did not have a withdrawal menses in at least one of 6 cycles of use.

Some women may experience post-pill amenorrhea or oligomenorrhea (possibly with anovulation), especially when such a condition was preexistent.

PRECAUTIONS

1. SEXUALLY TRANSMITTED DISEASES

Patients should be counseled that this product does not protect against HIV infection (AIDS) and other sexually transmitted diseases.

2. PHYSICAL EXAMINATION AND FOLLOW-UP

A periodic personal and family medical history and complete physical examination are appropriate for all women, including women using oral contraceptives. The physical examination, however, may be deferred until after initiation of oral contraceptives if requested by the woman and judged appropriate by the clinician. The physical examination should include special reference to blood pressure, breasts, abdomen and pelvic organs, including cervical cytology, and relevant laboratory tests. In case of undiagnosed, persistent or recurrent abnormal vaginal bleeding, appropriate measures should be conducted to rule out malignancy. Women with a strong family history of breast cancer or who have breast nodules should be monitored with particular care.

3. LIPID DISORDERS

Women who are being treated for hyperlipidemias should be followed closely if they elect to use oral contraceptives. Some progestogens may elevate LDL levels and may render the control of hyperlipidemias more difficult. (See WARNINGS 1.d.).

In patients with familial defects of lipoprotein metabolism receiving estrogen-containing preparations, there have been case reports of significant elevations of plasma triglycerides leading to pancreatitis.

4. LIVER FUNCTION

If jaundice develops in any woman receiving such drugs, the medication should be discontinued. Steroid hormones may be poorly metabolized in patients with impaired liver function.

5. FLUID RETENTION

Oral contraceptives may cause some degree of fluid retention. They should be prescribed with caution, and only with careful monitoring, in patients with conditions which might be aggravated by fluid retention.

6. EMOTIONAL DISORDERS

Women with a history of depression should be carefully observed and the drug discontinued if depression recurs to a serious degree. Patients becoming significantly depressed while taking oral contraceptives should stop the medication and use an alternate method of contraception in an attempt to determine whether the symptom is drug related. Women with a history of depression should be carefully observed and the drug discontinued if depression recurs to a serious degree.

7. CONTACT LENSES

Contact lens wearers who develop visual changes or changes in lens tolerance should be assessed by an ophthalmologist.

8. DRUG INTERACTIONS

Changes in contraceptive effectiveness associated with co-administration of other products:

a. Anti-infective agents and anticonvulsants

Contraceptive effectiveness may be reduced when hormonal contraceptives are co-administered with antibiotics, anticonvulsants, and other drugs that increase the metabolism of contraceptive steroids. This could result in unintended pregnancy or breakthrough bleeding. Examples include rifampin, barbiturates, phenylbutazone, phenytoin, carbamazepine, felbamate, oxcarbazepine, topiramate, and griseofulvin.

b. Anti-HIV protease inhibitors

Several of the anti-HIV protease inhibitors have been studied with co-administration of oral combination hormonal contraceptives; significant changes (increase and decrease) in the plasma levels of the estrogen and progestin have been noted in some cases. The safety and efficacy of combination oral contraceptive products may be affected with co-administration of anti-HIV protease inhibitors. Healthcare providers should refer to the label of the individual anti-HIV protease inhibitors for further drug-drug interaction information.

c. Herbal products

Herbal products containing St. John’s Wort (hypericum perforatum) may induce hepatic enzymes (cytochrome P450) and p-glycoprotein transporter and may reduce the effectiveness of contraceptive steroids. This may also result in breakthrough bleeding.

Increase in plasma levels of estradiol associated with co-administered drugs:

Co-administration of atorvastatin and certain combination oral contraceptives containing ethinyl estradiol increase AUC values for ethinyl estradiol by approximately 20%. Ascorbic acid and acetaminophen may increase plasma ethinyl estradiol levels, possibly by inhibition of conjugation. CYP3A4 inhibitors such as itraconazole or ketoconazole may increase plasma hormone levels.

Changes in plasma levels of co-administered drugs:

Combination hormonal contraceptives containing some synthetic estrogens (e.g., ethinyl estradiol) may inhibit the metabolism of other compounds. Increased plasma concentrations of cyclosporine, prednisolone, and theophylline have been reported with concomitant administration of combination oral contraceptives. Decreased plasma concentrations of acetaminophen and increased clearance of temazepam, salicylic acid, morphine and clofibric acid, due to induction of conjugation have been noted when these drugs were administered with combination oral contraceptives.

9. INTERACTIONS WITH LABORATORY TESTS

Certain endocrine and liver function tests and blood components may be affected by oral contraceptives:

1. Increased prothrombin and factors VII, VIII, IX, and X; decreased antithrombin 3; increased norepinephrine-induced platelet aggregability.
2. Increased thyroid-binding globulin (TBG) leading to increased circulating total thyroid hormone, as measured by protein-bound iodine (PBI), T4 by column or by radioimmunoassay. Free T3 resin uptake is decreased, reflecting the elevated TBG, free T4 concentration is unaltered.
3. Other binding proteins may be elevated in serum.
4. Sex hormone binding globulins are increased and result in elevated levels of total circulating sex steroids and corticoids; however, free or biologically active levels remain unchanged.
5. Triglycerides may be increased and levels of various other lipids and lipoproteins may be affected.
6. Glucose tolerance may be decreased.
7. Serum folate levels may be depressed by oral contraceptive therapy. This may be of clinical significance if a woman becomes pregnant shortly after discontinuing oral contraceptives.

10. CARCINOGENESIS

See WARNINGS section.

11. PREGNANCY

Pregnancy Category X. See CONTRAINDICATIONS and WARNINGS sections.

12. NURSING MOTHERS

Small amounts of oral contraceptive steroids and/or metabolites have been identified in the milk of nursing mothers and a few adverse effects on the child have been reported, including jaundice and breast enlargement. In addition, combination oral contraceptives given in the postpartum period may interfere with lactation by decreasing the quantity and quality of breast milk. If possible, the nursing mother should be advised not to use combination oral contraceptives but to use other forms of contraception until she has completely weaned her child.

13. PEDIATRIC USE

Safety and efficacy of Loestrin 24 Fe have been established in women of reproductive age. Safety and efficacy are expected to be the same in postpubertal adolescents under the age of 16 years and in users age 16 years and older. Use of this product before menarche is not indicated.

14. GERIATRIC USE

This product has not been studied in women over 65 years of age and is not indicated in this population.

INFORMATION FOR THE PATIENT

See Patient Labeling printed below.

ADVERSE REACTIONS

The most common adverse events reported by 2 - 6% of the 743 women using Loestrin 24 Fe were the following, in order of decreasing incidence: headache, vaginal candidiasis, upper respiratory infection, nausea, menstrual cramps, breast tenderness, sinusitis, vaginitis (bacterial), abnormal cervical smear, acne, urinary tract infection, mood swings, weight gain, vomiting, and metrorrhagia.

Among the 743 women using Loestrin 24 Fe, 46 women (6.2%) withdrew because of an adverse event. Adverse events occurring in 3 or more subjects leading to discontinuation of treatment were, in decreasing order: abnormal bleeding (0.9%), nausea (0.8%), menstrual cramps (0.4%), increased blood pressure (0.4%), and irregular bleeding (0.4%).

An increased risk of the following serious adverse reactions has been associated with the use of oral contraceptives (see WARNINGS section):

- Thrombophlebitis
- Arterial thromboembolism
- Pulmonary embolism
- Myocardial infarction
- Cerebral hemorrhage
- Cerebral thrombosis
- Hypertension
- Gallbladder disease
- Hepatic adenomas or benign liver tumors

There is evidence of an association between the following conditions and the use of oral contraceptives:

- Mesenteric thrombosis
- Retinal thrombosis

The following adverse reactions have been reported in patients receiving oral contraceptives and are believed to be drug related:

- Nausea
- Vomiting
- Gastrointestinal symptoms (such as abdominal pain, cramps and bloating)
- Breakthrough bleeding
- Spotting
- Change in menstrual flow
- Amenorrhea
- Temporary infertility after discontinuation of treatment
- Edema/fluid retention
- Melasma/chloasma which may persist
- Breast changes: tenderness, pain, enlargement, and secretion
- Change in weight or appetite (increase or decrease)
- Change in cervical ectropion and secretion
- Possible diminution in lactation when given immediately postpartum
- Cholestatic jaundice
- Migraine headache
- Rash (allergic)
- Mood changes, including depression
- Vaginitis, including candidiasis
- Change in corneal curvature (steepening)
- Intolerance to contact lenses
- Decrease in serum folate levels
- Exacerbation of systemic lupus erythematosus
- Exacerbation of porphyria
- Exacerbation of chorea
- Aggravation of varicose veins
- Anaphylactic/anaphylactoid reactions, including urticaria, angioedema, and severe reactions with respiratory and circulatory symptoms

The following adverse reactions have been reported in users of oral contraceptives, and a causal association has been neither confirmed nor refuted:

- Acne
- Budd-Chiari syndrome
- Cataracts
- Colitis
- Changes in libido
- Cystitis-like syndrome
- Dizziness
- Dysmenorrhea
- Erythema multiforme
- Erythema nodosum
- Headache
- Hemorrhagic eruption
- Hemolytic uremic syndrome
- Hirsutism
- Impaired renal function
- Loss of scalp hair
- Nervousness
- Optic neuritis, which may lead to partial or complete loss of vision
- Pancreatitis
- Premenstrual syndrome

OVERDOSAGE

Serious ill effects have not been reported following acute ingestion of large doses of oral contraceptives by young children. Overdosage may cause nausea, and withdrawal bleeding may occur in females.

NONCONTRACEPTIVE HEALTH BENEFITS

The following noncontraceptive health benefits related to the use of oral contraceptives are supported by epidemiological studies which largely utilized oral-contraceptive formulations containing doses exceeding 0.035 mg of ethinyl estradiol or 0.05 mg of mestranol.

Effects on menses:

- Increased menstrual cycle regularity
- Decreased blood loss and decreased incidence of iron-deficiency anemia
- Decreased incidence of dysmenorrhea

Effects related to inhibition of ovulation:

- Decreased incidence of functional ovarian cysts
- Decreased incidence of ectopic pregnancies

Effects from long-term use:

- Decreased incidence of fibroadenomas and fibrocystic disease of the breast
- Decreased incidence of acute pelvic inflammatory disease
- Decreased incidence of endometrial cancer
- Decreased incidence of ovarian cancer

DOSAGE AND ADMINISTRATION

To achieve maximum contraceptive effectiveness, Loestrin 24 Fe should be taken exactly as directed and at intervals not exceeding 24 hours. Loestrin 24 Fe tablets may be administered without regard to meals.

Loestrin 24 Fe provides a regimen consisting of 24 white active tablets of Loestrin 24 Fe and 4 brown non-hormonal (placebo) tablets of ferrous fumarate. The ferrous fumarate tablets do not serve any therapeutic purpose.

During the first cycle of use:

The possibility of ovulation and conception prior to initiation of medication should be considered. The patient is instructed to begin taking Loestrin 24 Fe on either Day 1 of menstruation (Day 1 Start) or the first Sunday after the onset of menstruation (Sunday Start). If menstruation begins on a Sunday, the first tablet (white) is taken that day. One white tablet should be taken daily for 24 consecutive days followed by one brown tablet daily for 4 consecutive days. Withdrawal bleeding should usually occur within three days following discontinuation of white tablets and may not have finished before the next pack is started. During the first cycle with a Sunday start, contraceptive reliance should not be placed on Loestrin 24 Fe until a white tablet has been taken daily for 7 consecutive days and a non-hormonal back-up method of birth control (such as condoms or spermicide) should be used during those 7 days.

The patient begins her next and all subsequent 28-day courses of tablets on the same day of the week on which she began her first course, following the same schedule: 24 days on white tablets—4 days on brown tablets. If in any cycle the patient starts tablets later than the proper day, she should protect herself against pregnancy by using a non-hormonal back-up method of birth control until she has taken a white tablet daily for 7 consecutive days.

Switching from another hormonal method of contraception:

When the patient is switching to Loestrin 24 Fe after completing a 21-day regimen of oral contraceptive tablets, transdermal patches, or a vaginal ring, she should wait 7 days after her last tablet, patch, or ring before she starts Loestrin 24 Fe. She will probably experience withdrawal bleeding during that week. She should be sure that no more than 7 days pass after her previous 21-day regimen. When the patient is switching to Loestrin 24 Fe after completing a 28-day regimen of oral contraceptive tablets, she should start her first pack of Loestrin 24 Fe on the day after her last tablet. She should not wait any days between packs. The patient may switch any day from a progestin-only pill and should begin Loestrin 24 Fe the next day. If switching from an implant or injection, the patient should start Loestrin 24 Fe on the day of implant removal or, if using an injection, the day the next injection would be due.

If spotting or breakthrough bleeding occurs:

The patient is instructed to continue on the same regimen. This type of bleeding is usually transient and without significance; however, if the bleeding is persistent or prolonged, the patient is advised to consult her healthcare provider. Although pregnancy is unlikely if Loestrin 24 Fe is taken according to directions, if withdrawal bleeding does not occur, the possibility of pregnancy must be considered. If the patient has not adhered to the prescribed schedule (missed one or more tablets or started taking them on a day later than she should have), the probability of pregnancy should be considered at the time of the first missed period and appropriate diagnostic measures taken. If the patient has adhered to the prescribed regimen and misses two consecutive periods, pregnancy should be ruled out. Hormonal contraceptives should be discontinued if pregnancy is confirmed.

For additional patient instructions regarding missed pills:

See the “WHAT TO DO IF YOU MISS PILLS” section in the DETAILED PATIENT LABELING. Any time the patient misses two or more white tablets, she should also use another method of non-hormonal back-up contraception until she has taken a white tablet daily for seven consecutive days. If the patient misses one or more brown tablets, she is still protected against pregnancy provided she begins taking the active white tablets again on the proper day. If breakthrough bleeding occurs following missed white tablets, it will usually be transient and of no consequence. The possibility of ovulation increases with each successive day that scheduled white tablets are missed. Therefore, the risk of pregnancy increases with each active (white) tablet missed.

Use after pregnancy, abortion or miscarriage:

Loestrin 24 Fe should be initiated no earlier than 28 days postpartum in the nonlactating mother due to the increased risk for thromboembolism. When the tablets are administered in the postpartum period, the increased risk of thromboembolic disease associated with the postpartum period must be considered (see CONTRAINDICATIONS, WARNINGS, and PRECAUTIONS concerning thromboembolic disease). The patient should be advised to use a non-hormonal back-up method for the first 7 days of tablet taking. However, if intercourse has already occurred, the possibility of ovulation and conception prior to initiation of medication should be considered.

Loestrin 24 Fe may be initiated after a first-trimester abortion or miscarriage; if the patient starts Loestrin 24 Fe immediately, additional contraceptive measures are not needed.

For additional patient instructions regarding complete dosing instructions, see the “HOW TO TAKE THE PILL” section in the DETAILED PATIENT LABELING.

HOW SUPPLIED

Loestrin® 24 Fe is available in blister cards (dispensers) containing 24 white active tablets and 4 brown placebo tablets. Each white, round tablet contains 1 mg of norethindrone acetate and 20 mcg of ethinyl estradiol and is imprinted with WC on one side and 530 on the other. Each brown, round tablet contains 75 mg ferrous fumarate.

NDC 54868-6100-0 - blister cards

Rx only

Keep this drug and all drugs out of the reach of children.
Store at 25° C (77° F); excursions permitted to 15 - 30° C (59 - 86° F) [see USP Controlled Room Temperature].

References are available upon request.

PATIENT BRIEF SUMMARY

This product (like all oral contraceptives) is intended to prevent pregnancy. It does not protect against HIV infection (AIDS) and other sexually transmitted diseases.

Oral contraceptives, also known as "birth control pills" or "the pill", are taken to prevent pregnancy, and when taken correctly without missing any pills, have a failure rate of about 1% per year (1 pregnancy per 100 women per year of use). The typical failure rate of pill users is 5% (5 pregnancies per 100 women per year of use) when women who miss pills are included.

For the majority of women, oral contraceptives can be taken safely. But for some women oral contraceptive use is associated with certain serious medical problems that can be life-threatening or may cause temporary or permanent disability or death. The risks associated with taking oral contraceptives increase significantly if you:

- Smoke
- Have high blood pressure, diabetes, high cholesterol, or are obese
- Have or have had clotting disorders, heart attack, stroke, angina pectoris (severe chest pains), cancer of the breast or sex organs, jaundice, or malignant or benign liver tumors

You should not take the pill if you are pregnant or have unexplained vaginal bleeding.

Although cardiovascular disease risks may be increased with oral contraceptive use after age 40 in healthy, non-smoking women (even with the newer low-dose formulations), there are also greater potential health risks associated with pregnancy in older women.

Cigarette smoking increases the risk of serious adverse effects on the heart and blood vessels from oral contraceptive use. This risk increases with age and with the amount of smoking (15 or more cigarettes per day has been associated with a significantly increased risk) and is quite marked in women over 35 years of age. Women who use oral contraceptives should not smoke.

Most side effects of the pill are not serious. The most common are nausea, vomiting, bleeding or spotting between menstrual periods, weight gain, breast tenderness, and difficulty wearing contact lenses. These side effects, especially nausea and vomiting, may decrease or subside within the first three months of use.

The serious side effects of the pill occur very infrequently, especially if you are in good health and do not smoke. However, you should know that the following medical conditions have been associated with or made worse by the pill:

1. Blood clots in the legs (thrombophlebitis), lungs (pulmonary embolism), stoppage or rupture of a blood vessel in the brain (stroke), blockage of blood vessels in the heart (heart attack or angina pectoris), or other organs of the body. As mentioned above, smoking increases the risk of heart attacks and strokes and subsequent serious medical consequences. Women with migraine headaches also may be at increased risk of stroke when taking the pill.

2. Liver tumors, which may rupture and cause severe bleeding. A possible but not definite association has been found with the pill and liver cancer. However, liver cancers are extremely rare. The chance of developing liver cancer from using the pill is thus even rarer.

3. High blood pressure, although blood pressure usually returns to normal when the pill is stopped.

The symptoms associated with these serious side effects are discussed in the DETAILED PATIENT INFORMATION leaflet given to you with your supply of pills. Notify your healthcare provider if you notice any unusual physical disturbances while taking the pill. In addition, drugs such as rifampin, as well as some anticonvulsants and some antibiotics, and herbal preparations containing St. John's Wort (hypericum perforatum), may decrease oral contraceptive effectiveness.

Breast cancer has been diagnosed slightly more often in women who use the pill than in women of the same age who do not use the pill. This very small increase in the number of breast cancer diagnoses gradually disappears during the 10 years after stopping use of the pill. It is not known whether the difference is caused by the pill. It may be that women taking the pill are examined more often, so that breast cancer is more likely to be detected. You should have regular breast examinations by a healthcare provider and examine your own breasts monthly. Tell your healthcare provider if you have a family history of breast cancer or if you have had breast nodules or an abnormal mammogram. Women who currently have or have had breast cancer should not use hormonal contraceptives because breast cancer is usually a hormone-sensitive tumor.

Some studies have found an increase in the incidence of cancer or precancerous lesions of the cervix in women who use the pill. However, this finding may be related to factors other than the use of the pill.

Taking the combination pill provides some important noncontraceptive health benefits. These include less painful menstruation, less menstrual blood loss and anemia, fewer pelvic infections, and fewer cancers of the ovary and the lining of the uterus.

Be sure to discuss any medical condition you may have with your healthcare provider. Your healthcare provider will take a medical and family history before prescribing oral contraceptives and will examine you. The physical examination may be delayed to another time if you request it and the healthcare provider believes that it is a good medical practice to postpone it. You should be reexamined at least once a year while taking oral contraceptives. The DETAILED PATIENT INFORMATION leaflet gives you further information which you should read and discuss with your healthcare provider.

DOSAGE AND ADMINISTRATION

HOW TO TAKE Loestrin 24 Fe

IMPORTANT POINTS TO REMEMBER

BEFORE YOU START TAKING YOUR PILLS:

1. BE SURE TO READ THESE DIRECTIONS:
  - Before you start taking your pills
  - Anytime you are not sure what to do
2. TAKE ONE PILL EVERY DAY AT THE SAME TIME.
  If you miss pills you could get pregnant. This includes starting the pack late. The more pills you miss, the more likely you are to get pregnant.
3. MANY WOMEN HAVE SPOTTING OR LIGHT BLEEDING, OR MAY FEEL SICK TO THEIR STOMACH WHILE TAKING THE FIRST 1 to 3 PACKS OF PILLS.
  If you have spotting or light bleeding or feel sick to your stomach, do not stop taking the pill. The problem will usually go away. If it doesn't go away, check with your healthcare provider.
4. MISSING PILLS CAN ALSO CAUSE SPOTTING OR LIGHT BLEEDING, even if you take these missed pills. On the days you take 2 pills to make up for missed pills, you could also feel a little sick to your stomach.
5. IF YOU HAVE VOMITING (within 3 to 4 hours after you take your pill), you should follow the instructions for WHAT TO DO IF YOU MISS PILLS. IF YOU HAVE DIARRHEA or IF YOU TAKE CERTAIN MEDICINES, including some antibiotics, or the herbal supplement St. John’s Wort, your pills may not work as well. Use a back-up method of birth control (such as condoms or spermicide) until you check with your healthcare provider.
6. IF YOU HAVE TROUBLE REMEMBERING TO TAKE THE PILL, talk to your healthcare provider about how to make pill-taking easier or about using another method of birth control.
7. IF YOU HAVE ANY QUESTIONS OR ARE UNSURE ABOUT THE INFORMATION IN THIS LEAFLET, call your healthcare provider.

BEFORE YOU START TAKING YOUR PILLS

1. DECIDE WHAT TIME OF DAY YOU WANT TO TAKE YOUR PILL.
It is important to take it at about the same time every day.

2. LOOK AT YOUR PILL PACK:

Loestrin 24 Fe contains 24 "active" WHITE PILLS (with hormones) for WEEKS 1, 2, 3 and the first part of WEEK 4, and 4 "reminder" BROWN PILLS (without hormones) for the last part of WEEK 4.

3. ALSO FIND:

- where on the pack to start taking pills,
- in what order to take the pills (follow the arrows), and
- the week numbers as shown in the picture above.

4. BE SURE YOU HAVE READY AT ALL TIMES:

- ANOTHER KIND OF BIRTH CONTROL (such as condoms or spermicide) to use as a back-up in case you miss pills.
- AN EXTRA, PILL PACK.

WHEN TO START THE FIRST PACK OF PILLS

You have a choice of which day to start taking your first pack of pills. Decide with your healthcare provider which is the best day for you. Pick a time of day that will be easy to remember.

DAY-1 START:

1. Pick the day label strip that starts with the first day of your period. (This is the day you start bleeding or spotting, even if it is almost midnight when the bleeding begins.)
2. Place this day label strip on the tablet dispenser over the area that has the days of the week (starting with Sunday) printed on the plastic.
3. Take the first white pill of the first pack during the first 24 hours of your period.
4. You will not need to use a back-up method of birth control, since you are starting the pill at the beginning of your period.

SUNDAY START:

1. Take the first white pill of the first pack on the Sunday after your period starts, even if you are still bleeding. If your period begins on Sunday, start the pack that same day.
2. Use another method of birth control as a back-up method if you have sex anytime from the Sunday you start your first pack until the next Sunday (7 days). Condoms or spermicide are good back-up methods of birth control.

WHEN YOU SWITCH FROM A DIFFERENT METHOD OF HORMONAL CONTRACEPTION

- If your previous method had 28 pills, finish taking all 28 pills, then start taking Loestrin 24 Fe on the day after the last pill.
- If your previous method had 21 pills, finish taking all 21 pills, and wait 7 days before starting Loestrin 24 Fe.
- When you switch from a vaginal ring or skin patch, finish the 21 days of use, and wait 7 days after removal of the ring or patch before starting Loestrin 24 Fe.
- When you switch from a progestin-only pill, you should start Loestrin 24 Fe the next day.
- When you switch from an implant or injectable contraceptive, you should start Loestrin 24 Fe on the day of implant removal or, if using an injectable contraceptive, the day on which the next injection would be due.

WHAT TO DO DURING THE MONTH

1. TAKE ONE PILL AT THE SAME TIME EVERY DAY UNTIL THE PACK IS EMPTY. Do not skip pills even if you are spotting or bleeding between monthly periods or feel sick to your stomach (nausea). Do not skip pills even if you do not have sex very often.
2. WHEN YOU FINISH A PACK OF YOUR Loestrin 24 Fe: Start the next pack on the day after your last brown “reminder" pill. Do not wait any days between packs.

WHAT TO DO IF YOU MISS PILLS

Birth control pills may not be as effective if you miss any white pills, and particularly if you miss the first few or the last few white pills in a pack.

If you MISS 1 white pill:

1. Take it as soon as you remember. Take the next pill at your regular time. This means you may take 2 pills in 1 day.
2. You do not need to use a back-up birth control method if you have sex.

If you MISS 2 white pills in a row in WEEK 1 OR WEEK 2 of your pack:

1. Take 2 pills on the day you remember and 2 pills the next day.
2. Then take 1 pill a day until you finish the pack.
3. You COULD BECOME PREGNANT if you have sex during the 7 days after you restart your pills. You MUST use a non-hormonal birth control method (such as condoms or spermicide) as a back-up for those 7 days.

If you MISS 2 white pills in a row in WEEK 3 or WEEK 4 of your pack:

1. 1.If you are a Day 1 Starter:
  THROW OUT the rest of the pill pack and start a new pack that same day.
  If you are a Sunday Starter:
  Keep taking 1 pill every day until Sunday.
  On Sunday, THROW OUT the rest of the pack and start a new pack of pills that same day.
2. You may not have your period this month but this is expected. However, if you miss your period 2 months in a row, call your healthcare provider because you might be pregnant.
3. You COULD BECOME PREGNANT if you have sex during the 7 days after you restart your pills. You MUST use a non-hormonal birth control method (such as condoms or spermicide) as a back-up for those 7 days after you restart your pills.

If you MISS 3 OR MORE white pills in a row at any time:

1. If you are a Day 1 Starter:
  THROW OUT the rest of the pill pack and start a new pack that same day.
  If you are a Sunday Starter:
  Keep taking 1 pill every day until Sunday.
  On Sunday, THROW OUT the rest of the pack and start a new pack of pills that same day.
2. You may not have your period this month but this is expected. However, if you miss your period 2 months in a row, call your healthcare provider because you might be pregnant.
3. You COULD BECOME PREGNANT if you have sex on the days when you missed pills or during the first 7 days after restarting your pills. You MUST use a non-hormonal birth control method (such as condoms or spermicide) as a back-up the next time you have sex and for the first 7 days after you restart your pills.

If you forget any of the 4 brown "reminder" pills in Week 4:

1. THROW AWAY the pills you missed.
2. Keep taking 1 pill each day until the pack is empty.
3. You do not need to use a back-up method of birth control.

FINALLY, IF YOU ARE STILL NOT SURE WHAT TO DO ABOUT THE PILLS YOU HAVE MISSED:

1. Use a BACK-UP METHOD of birth control anytime you have sex.
2. KEEP TAKING ONE WHITE PILL EACH DAY until you can reach your healthcare provider.

DETAILED PATIENT PACKAGE INSERT

This product (like all oral contraceptives) is intended to prevent pregnancy. It does not protect against HIV infection (AIDS) and other sexually transmitted diseases.

INTRODUCTION

Any woman who considers using oral contraceptives (the “birth control pill” or “the pill”) should understand the benefits and risks of using this form of birth control.

Although oral contraceptives have important advantages over other methods of contraception, they have certain risks that no other method has, and some of these risks may continue after you have stopped using the oral contraceptive. This leaflet will give you much of the information you will need to make this decision and will also help you determine if you are at risk of developing any of the serious side effects of the pill. It will tell you how to use Loestrin 24 Fe properly so that it will be as effective as possible. However, this booklet is not a replacement for a careful discussion between you and your healthcare provider. You should discuss the information provided in this booklet with your healthcare provider, both when you first start taking the pill and during your revisits. You should also follow your healthcare provider’s advice with regard to regular check-ups while you are on Loestrin 24 Fe.

EFFECTIVENESS OF ORAL CONTRACEPTIVES

Oral contraceptives or “birth control pill” or “the pill” are used to prevent pregnancy and are more effective than most other nonsurgical methods of birth control. The chance of becoming pregnant is approximately 1% per year (1 pregnancy per 100 women per year of use) when the pills are taken correctly, and no pills are missed. Typical failure rates are 5% per year when women who miss pills are included. The chance of becoming pregnant increases with each missed "active" hormonal pill during a 28-day cycle.

In comparison, typical failure rates for other methods of birth control during the first year of use are as follows:

No birth control methods: 85%
Vaginal sponge: 20 to 40%
Cervical cap: 20 to 40%
Spermicides alone: 26%
Periodic abstinence: 25%
Condom (female): 21%
Diaphragm with spermicides: 20%
Withdrawal: 19%
Condom (male): 14%
Female sterilization: less than 1%
IUD: less than 1-2%
Injectable progestogen: less than 1%
Male sterilization: less than 1%
Norplant® system: less than 1%

WHO SHOULD NOT TAKE ORAL CONTRACEPTIVES

Cigarette smoking increases the risk of serious adverse effects on the heart and blood vessels from oral contraceptive use. This risk increases with age and with the amount of smoking (15 or more cigarettes per day has been associated with a significantly increased risk) and is quite marked in women over 35 years of age. Women who use oral contraceptives should not smoke.

Some women should not use the pill. You should not use the pill if you have or have ever had any of the following conditions:

- A history of heart attack or stroke
- A history of blood clots in the legs (thrombophlebitis), lungs (pulmonary embolism), or eyes
- A history of blood clots in the deep veins of your legs
- Chest pain (angina pectoris)
- Known or suspected breast cancer or cancer of the lining of the uterus, cervix, vagina, or certain hormonally-sensitive cancers
- Unexplained vaginal bleeding (until a diagnosis is reached by your healthcare provider)
- Yellowing of the whites of the eyes or of the skin (jaundice) during pregnancy or during previous use of hormonal contraceptives of any type (the pill, patch, vaginal ring, injection, or implant)
- Liver tumor (benign or cancerous)
- Known or suspected pregnancy
- Heart valve or heart rhythm disorders that may be associated with formation of blood clots
- Diabetes with complications of the kidneys, eyes, nerves, or blood vessels
- Severe high blood pressure
- Active liver disease with abnormal liver function tests
- Allergy or hypersensitivity to any of the components of Loestrin 24 Fe
- A need for surgery with prolonged bedrest
- Headaches with neurological symptoms

Tell your healthcare provider if you have any of the above conditions. Your healthcare provider can recommend a safer method of birth control.

OTHER CONSIDERATIONS BEFORE TAKING ORAL CONTRACEPTIVES

Tell your healthcare provider if you have or ever have had:

- Breast nodules, fibrocystic disease of the breast or an abnormal breast x-ray or mammogram
- Diabetes
- Elevated cholesterol or triglycerides
- High blood pressure
- Migraine or other headaches or epilepsy
- Depression
- Gallbladder, liver, heart, or kidney disease
- Scanty or irregular menstrual periods

Women with any of these conditions should be checked often by their healthcare provider if they choose to use oral contraceptives.

Talk to your healthcare provider about using Loestrin 24 Fe if you:

- Smoke
- Recently had a baby
- Recently had a miscarriage or abortion
- Are breastfeeding
- Are taking any other medications

RISKS OF TAKING ORAL CONTRACEPTIVES

1. Risk of developing blood clots

Blood clots and blockage of blood vessels are the most serious side effects of taking oral contraceptives and can cause death or serious disability. In particular, a clot in the legs can cause thrombophlebitis, and a clot that travels to the lungs can cause a sudden blocking of the vessel carrying blood to the lungs. Either of these can cause death or disability. Rarely, clots occur in the blood vessels of the eye and may cause blindness, double vision, or impaired vision.

If you take oral contraceptives and need elective surgery, need to stay in bed for a prolonged illness or injury, or have recently delivered a baby, you may be at risk of developing blood clots. You should consult your healthcare provider about stopping oral contraceptives four weeks before surgery and not taking oral contraceptives for two weeks after surgery or during bed rest. You should also not take oral contraceptives soon after delivery of a baby. It is advisable to wait for at least four weeks after delivery if you are not breastfeeding. If you are breastfeeding, you should wait until you have weaned your child before using the pill (see the section on breastfeeding in GENERAL PRECAUTIONS).

The risk of circulatory disease in oral contraceptive users may be higher in users of high-dose pills (containing 50 micrograms or higher of ethinyl estradiol) and may be greater with longer duration of oral contraceptive use. In addition, some of these increased risks may continue for a number of years after stopping oral contraceptives. The risk of abnormal blood clotting increases with age in both users and nonusers of oral contraceptives, but the increased risk from the oral contraceptive appears to be present at all ages. For women aged 20 to 44 it is estimated that about 1 in 2,000 using oral contraceptives will be hospitalized each year because of abnormal clotting. Among nonusers in the same age group, about 1 in 20,000 would be hospitalized each year. For oral contraceptive users in general, it has been estimated that in women between the ages of 15 and 34 the risk of death due to a circulatory disorder is about 1 in 12,000 per year, whereas for nonusers the rate is about 1 in 50,000 per year. In the age group 35 to 44, the risk is estimated to be about 1 in 2,500 per year for oral contraceptive users and about 1 in 10,000 per year for nonusers.

2. Heart attacks and strokes

Oral contraceptives may increase the tendency to develop strokes (stoppage or rupture of blood vessels in the brain) and angina pectoris and heart attacks (blockage of blood vessels in the heart). Any of these conditions can cause death or disability.

Smoking greatly increases the possibility of suffering heart attacks and strokes. Furthermore, smoking and the use of oral contraceptives greatly increase the chances of developing and dying of heart disease.

Women with migraine (especially migraine with aura) who take oral contraceptives also may be at higher risk of stroke.

3. Gallbladder disease

Oral contraceptive users probably have a greater risk than nonusers of having gallbladder disease, although this risk may be related to pills containing high doses of estrogens.

4. Liver tumors

In rare cases, oral contraceptives can cause benign but dangerous liver tumors. These benign liver tumors can rupture and cause fatal internal bleeding. In addition, a possible, but not definite, association has been found with the pill and liver cancers in two studies, in which a few women who developed these very rare cancers were found to have used oral contraceptives for long periods. However, liver cancers in general are extremely rare, and the chance of developing liver cancer from using the pill is thus even rarer.

5. Cancer of the breast and reproductive organs

Breast cancer has been diagnosed slightly more often in women who use the pill than in women of the same age who do not use the pill. This small increase in the number of breast cancer diagnoses gradually disappears during the 10 years after stopping use of the pill. It is not known whether the difference is caused by the pill. It may be that women taking the pill are examined more often, so that breast cancer is more likely to be detected. You should have regular breast examinations by a healthcare provider and examine your own breasts monthly. Tell your healthcare provider if you have a family history of breast cancer or if you have had breast nodules or an abnormal mammogram.

Women who currently have or have had breast cancer should not use oral contraceptives because breast cancer is usually a hormone-sensitive tumor.

Some studies have found an increase in the incidence of cancer or precancerous lesions of the cervix in women who use oral contraceptives. However, this finding may be related to factors other than the use of oral contraceptives. There is insufficient evidence to rule out the possibility that the pill may cause such cancers.

6. Lipid metabolism and inflammation of the pancreas

In patients with inherited defects of lipid metabolism, there have been reports of significant elevations of plasma triglycerides during estrogen therapy. This has led to pancreatitis in some cases.

ESTIMATED RISK OF DEATH FROM A BIRTH CONTROL METHOD OR PREGNANCY

All methods of birth control and pregnancy are associated with a risk of developing certain diseases which may lead to disability or death. An estimate of the number of deaths associated with different methods of birth control and pregnancy has been calculated and is shown in the following table.

ANNUAL NUMBER OF BIRTH-RELATED OR METHOD-RELATED DEATHS ASSOCIATED WITH CONTROL OF FERTILITY PER 100,000 NONSTERILE WOMEN, BY FERTILITY CONTROL METHOD ACCORDING TO AGE
 |  |  | AGE
Method of control and outcome | 15-19 | 20-24 | 25-29 | 30-34 | 35-39 | 40-44
No fertility control methods* | 7.0 | 7.4 | 9.1 | 14.8 | 25.7 | 28.2
Oral contraceptives nonsmoker† | 0.3 | 0.5 | 0.9 | 1.9 | 13.8 | 31.6
Oral contraceptives smoker† | 2.2 | 3.4 | 6.6 | 13.5 | 51.1 | 117.2
IUD† | 0.8 | 0.8 | 1.0 | 1.0 | 1.4 | 1.4
Condom* | 1.1 | 1.6 | 0.7 | 0.2 | 0.3 | 0.4
Diaphragm/spermicide* | 1.9 | 1.2 | 1.2 | 1.3 | 2.2 | 2.8
Periodic abstinence* | 2.5 | 1.6 | 1.6 | 1.7 | 2.9 | 3.6

* Deaths are birth related
† Deaths are method related

In the above table, the risk of death from any birth control method is less than the risk of childbirth, except for oral contraceptive users over the age of 35 who smoke and pill users over the age of 40 even if they do not smoke. It can be seen in the table that for women aged 15 to 39, the risk of death was highest with pregnancy (7 to 26 deaths per 100,000 women, depending on age). Among pill users who do not smoke, the risk of death was always lower than that associated with pregnancy for any age group less than 40. Over the age of 40, the risk increases to 32 deaths per 100,000 women, compared to 28 deaths associated with pregnancy in that age group. However, for pill users who smoke and are over the age of 35, the estimated number of deaths exceeds those associated with pregnancy. If a woman is over the age of 40 and smokes, her estimated risk of death is four times higher (117/100,000 women) than the estimated risk associated with pregnancy (28/100,000 women) in that age group.

The suggestion that women over 40 who don't smoke should not take oral contraceptives is based on information from older high-dose pills. An Advisory Committee of the FDA discussed this issue in 1989 and recommended that the benefits of oral contraceptive use by healthy, nonsmoking women over 40 years of age may outweigh the possible risks. Older women, as all women who take oral contraceptives, should take an oral contraceptive which contains the least amount of estrogen and progestin that is compatible with the individual patient needs.

WARNING SIGNALS

If any of these adverse conditions occur while you are taking oral contraceptives, call your healthcare provider immediately:

- Sharp chest pain, coughing of blood, or sudden shortness of breath (indicating a possible clot in the lung)
- Pain in the calf (indicating a possible clot in the leg)
- Crushing chest pain or heaviness in the chest (indicating a possible heart attack)
- Sudden severe headache or vomiting, dizziness or fainting, disturbances of vision or speech, weakness, or numbness in an arm or leg (indicating a possible stroke)
- Sudden partial or complete loss of vision (indicating a possible clot in the eye)
- Breast lumps (indicating possible breast cancer or fibrocystic disease of the breast; ask your healthcare provider to show you how to examine your breasts)
- Severe pain or tenderness in the stomach area (possibly indicating a ruptured liver tumor)
- Difficulty in sleeping, weakness, lack of energy, fatigue, or change in mood (possibly indicating severe depression)
- Jaundice or a yellowing of the skin or eyeballs, accompanied frequently by fever, fatigue, loss of appetite, dark-colored urine, or light-colored bowel movements (indicating possible liver problems)

SIDE EFFECTS OF ORAL CONTRACEPTIVES

In addition to the risks and more serious side effects discussed above (see RISKS OF TAKING ORAL CONTRACEPTIVES, ESTIMATED RISK OF DEATH FROM A BIRTH CONTROL METHOD OR PREGNANCY and WARNING SIGNALS sections), the following may also occur:

1. Irregular vaginal bleeding

Irregular vaginal bleeding or spotting may occur while you are taking Loestrin 24 Fe Irregular bleeding may vary from slight staining between menstrual periods to breakthrough bleeding which is a flow much like a regular period. Irregular bleeding occurs most often during the first few months of oral contraceptive use, but may also occur after you have been taking the pill for some time. Such bleeding may be temporary and usually does not indicate any serious problems. It is important to continue taking your pills on schedule. If the bleeding occurs in more than one cycle or lasts for more than a few days, talk to your healthcare provider.

2. Contact lenses

If you wear contact lenses and notice a change in vision or an inability to wear your lenses, contact your healthcare provider.

3. Fluid retention or raised blood pressure

Oral contraceptives may cause edema (fluid retention) with swelling of the fingers or ankles and may raise your blood pressure. If you experience fluid retention, contact your healthcare provider.

4. Melasma

A spotty darkening of the skin is possible, particularly of the face. The darkening may persist after stopping the pill.

5. Other side effects

Other side effects may include nausea and vomiting, change in appetite, breast tenderness, headache, nervousness, depression, dizziness, loss of scalp hair, rash, vaginal infections, and allergic reactions.

If any of these side effects bother you, call your healthcare provider.

GENERAL PRECAUTIONS

1. Missed periods and use of oral contraceptives before or during early pregnancy

There may be times when you may not menstruate regularly after you have completed taking a cycle of pills. If you have taken your pills regularly and miss one menstrual period, continue taking your pills for the next cycle but be sure to inform your healthcare provider. If you have not taken the pills daily as instructed and missed a menstrual period, or if you missed two consecutive menstrual periods, you may be pregnant. Check with your healthcare provider immediately to determine whether you are pregnant. Stop taking Loestrin 24 Fe if you are pregnant.

There is no conclusive evidence that oral contraceptive use is associated with an increase in birth defects when taken inadvertently during early pregnancy. Previously, a few studies had reported that oral contraceptives might be associated with birth defects but these studies have not been confirmed. Nevertheless, oral contraceptives should not be used during pregnancy. You should check with your healthcare provider about risks to your unborn child of any medication taken during pregnancy.

2. While breastfeeding

If you are breastfeeding, consult your healthcare provider before starting oral contraceptives. Some of the drug will be passed on to the child in the milk. A few adverse effects on the child have been reported, including yellowing of the skin (jaundice) and breast enlargement. In addition, oral contraceptives may decrease the amount and quality of your milk. If possible, do not use oral contraceptives while breastfeeding. You should use another method of contraception since breastfeeding provides only partial protection from becoming pregnant, and this partial protection decreases significantly as you breastfeed for longer periods of time. You should consider starting oral contraceptives only after you have weaned your child completely.

3. Laboratory tests

If you are scheduled for any laboratory tests, tell your healthcare provider you are taking birth control pills. Certain blood tests may be affected by birth control pills.

4. Drug interactions

Certain drugs may interact with birth control pills to make them less effective in preventing pregnancy or cause an increase in breakthrough bleeding. Such drugs include rifampin, drugs used for epilepsy such as barbiturates (for example, phenobarbital), carbamazepine (Tegretol® is one brand of this drug), and phenytoin (Dilantin® is one brand of this drug), primidone (Mysoline®), topiramate (Topamax®), phenylbutazone (Butazolidin® is one brand), some drugs used for HIV such as ritonavir (Norvir®), modafinil (Provigil®) and possibly certain antibiotics (such as ampicillin and other penicillins, and tetracyclines). Pregnancies and breakthrough bleeding have been reported by users of combined hormonal contraceptives who also used some form of the herbal supplement St. John’s Wort. You may need to use a non-hormonal method of contraception during any cycle in which you take drugs that can make oral contraceptives less effective. Be sure to tell your healthcare provider if you are taking or start taking any other medications, including nonprescription products or herbal products while taking birth control pills.

You may be at higher risk of a specific type of liver dysfunction if you take troleandomycin (Tao® capsules) and oral contraceptives at the same time.

5. Sexually transmitted diseases

This product (like all oral contraceptives) is intended to prevent pregnancy. It does not protect against transmission of HIV (AIDS) and other sexually transmitted diseases such as Chlamydia, genital herpes, genital warts, gonorrhea, hepatitis B, and syphilis.

HOW TO TAKE Loestrin 24 Fe

IMPORTANT POINTS TO REMEMBER

BEFORE YOU START TAKING YOUR PILLS:

1. BE SURE TO READ THESE DIRECTIONS:
  - Before you start taking your pills
  - Anytime you are not sure what to do
2. TAKE ONE PILL EVERY DAY AT THE SAME TIME.
  If you miss pills you could get pregnant. This includes starting the pack late. The more pills you miss, the more likely you are to get pregnant.
3. MANY WOMEN HAVE SPOTTING OR LIGHT BLEEDING, OR MAY FEEL SICK TO THEIR STOMACH WHILE TAKING THE FIRST 1 to 3 PACKS OF PILLS.
  If you have spotting or light bleeding or feel sick to your stomach, do not stop taking the pill. The problem will usually go away. If it doesn't go away, check with your healthcare provider.
4. MISSING PILLS CAN ALSO CAUSE SPOTTING OR LIGHT BLEEDING, even if you take these missed pills. On the days you take 2 pills to make up for missed pills, you could also feel a little sick to your stomach.
5. IF YOU HAVE VOMITING (within 3 to 4 hours after you take your pill), you should follow the instructions for WHAT TO DO IF YOU MISS PILLS. IF YOU HAVE DIARRHEA or IF YOU TAKE CERTAIN MEDICINES, including some antibiotics, or the herbal supplement St. John’s Wort, your pills may not work as well. Use a back-up method of birth control (such as condoms or spermicide) until you check with your healthcare provider.
6. IF YOU HAVE TROUBLE REMEMBERING TO TAKE THE PILL, talk to your healthcare provider about how to make pill-taking easier or about using another method of birth control.
7. IF YOU HAVE ANY QUESTIONS OR ARE UNSURE ABOUT THE INFORMATION IN THIS LEAFLET, call your healthcare provider.

BEFORE YOU START TAKING YOUR PILLS

1. DECIDE WHAT TIME OF DAY YOU WANT TO TAKE YOUR PILL.
It is important to take it at about the same time every day.

2. LOOK AT YOUR PILL PACK:
Loestrin 24 Fe contains 24 "active" WHITE PILLS (with hormones) for WEEKS 1, 2, 3 and the first part of WEEK 4, and 4 "reminder" BROWN PILLS (without hormones) for the last part of WEEK 4.

3. ALSO FIND:

- where on the pack to start taking pills,
- in what order to take the pills (follow the arrows), and
- the week numbers as shown in the picture above.

4. BE SURE YOU HAVE READY AT ALL TIMES:

- ANOTHER KIND OF BIRTH CONTROL (such as condoms or spermicide) to use as a back-up in case you miss pills.
- AN EXTRA, PILL PACK.

WHEN TO START THE FIRST PACK OF PILLS

You have a choice of which day to start taking your first pack of pills. Decide with your healthcare provider which is the best day for you. Pick a time of day that will be easy to remember.

DAY-1 START:

1. Pick the day label strip that starts with the first day of your period. (This is the day you start bleeding or spotting, even if it is almost midnight when the bleeding begins.)
2. Place this day label strip on the tablet dispenser over the area that has the days of the week (starting with Sunday) printed on the plastic.
3. Take the first white pill of the first pack during the first 24 hours of your period.
4. You will not need to use a back-up method of birth control, since you are starting the pill at the beginning of your period.

SUNDAY START:

1. Take the first white pill of the first pack on the Sunday after your period starts, even if you are still bleeding. If your period begins on Sunday, start the pack that same day.
2. Use another method of birth control as a back-up method if you have sex anytime from the Sunday you start your first pack until the next Sunday (7 days). Condoms or spermicide are good back-up methods of birth control.

WHEN YOU SWITCH FROM A DIFFERENT METHOD OF HORMONAL CONTRACEPTION

- If your previous method had 28 pills, finish taking all 28 pills, then start taking Loestrin 24 Fe on the day after the last pill.
- If your previous method had 21 pills, finish taking all 21 pills, and wait 7 days before starting Loestrin 24 Fe.
- When you switch from a vaginal ring or skin patch, finish the 21 days of use, and wait 7 days after removal of the ring or patch before starting Loestrin 24 Fe.
- When you switch from a progestin-only pill, you should start Loestrin 24 Fe the next day.
- When you switch from an implant or injectable contraceptive, you should start Loestrin 24 Fe on the day of implant removal or, if using an injectable contraceptive, the day on which the next injection would be due.

WHAT TO DO DURING THE MONTH

1. TAKE ONE PILL AT THE SAME TIME EVERY DAY UNTIL THE PACK IS EMPTY.
  Do not skip pills even if you are spotting or bleeding between monthly periods or feel sick to your stomach (nausea).
  Do not skip pills even if you do not have sex very often.
2. WHEN YOU FINISH A PACK OF YOUR Loestrin 24 Fe:
  Start the next pack on the day after your last brown "reminder" pill. Do not wait any days between packs.

WHAT TO DO IF YOU MISS PILLS

Birth control pills may not be as effective if you miss any white pills, and particularly if you miss the first few or the last few white pills in a pack.

If you MISS 1 white pill:

1. Take it as soon as you remember. Take the next pill at your regular time. This means you may take 2 pills in 1 day.
2. You do not need to use a back-up birth control method if you have sex.

If you MISS 2 white pills in a row in WEEK 1 OR WEEK 2 of your pack:

1. Take 2 pills on the day you remember and 2 pills the next day.
2. Then take 1 pill a day until you finish the pack.
3. You COULD BECOME PREGNANT if you have sex during the 7 days after you restart your pills. You MUST use a non-hormonal birth control method (such as condoms or spermicide) as a back-up for those 7 days.

If you MISS 2 white pills in a row in WEEK 3 or Week 4 of your pack:

1. If you are a Day 1 Starter:
  THROW OUT the rest of the pill pack and start a new pack that same day.
  If you are a Sunday Starter:
  Keep taking 1 pill every day until Sunday.
  On Sunday, THROW OUT the rest of the pack and start a new pack of pills that same day.
2. You may not have your period this month but this is expected. However, if you miss your period 2 months in a row, call your healthcare provider because you might be pregnant.
3. You COULD BECOME PREGNANT if you have sex during the 7 days after you restart your pills. You MUST use a non-hormonal birth control method (such as condoms or spermicide) as a back-up for those 7 days after you restart your pills.

If you MISS 3 OR MORE white pills in a row at any time:

1. If you are a Day 1 Starter:
  THROW OUT the rest of the pill pack and start a new pack that same day.
  If you are a Sunday Starter:
  Keep taking 1 pill every day until Sunday.
  On Sunday, THROW OUT the rest of the pack and start a new pack of pills
  that same day.
2. You may not have your period this month but this is expected. However, if you miss your period 2 months in a row, call your healthcare provider because you might be pregnant.
3. You COULD BECOME PREGNANT if you have sex on the days when you missed pills or during the first 7 days after restarting your pills. You MUST use a non-hormonal birth control method (such as condoms or spermicide) as a back-up the next time you have sex and for the first 7 days after you restart your pills.

If you forget any of the 4 brown "reminder" pills in Week 4:

1. THROW AWAY the pills you missed.
2. Keep taking 1 pill each day until the pack is empty.
3. You do not need to use a back-up method of birth control.

FINALLY, IF YOU ARE STILL NOT SURE WHAT TO DO ABOUT THE PILLS YOU HAVE MISSED:

1. Use a BACK-UP METHOD of birth control anytime you have sex.
2. KEEP TAKING ONE WHITE PILL EACH DAY until you can reach your healthcare provider.

GENERAL

1. Pregnancy due to pill failure

If taken every day as directed, the incidence of pill failure resulting in pregnancy is approximately 1% per year (one pregnancy per 100 women per year), but more typical failure rates are about 5% per year. If pregnancy does occur, the risk to the fetus is minimal.

2. Pregnancy after stopping the pill

There may be some delay in becoming pregnant after you stop using oral contraceptives, especially if you had irregular menstrual cycles before you used oral contraceptives. It may be advisable to postpone conception until you begin menstruating regularly once you have stopped taking the pill and desire pregnancy.

There does not appear to be any increase in birth defects in newborn babies when pregnancy occurs soon after stopping the pill.

3. Overdosage

Serious ill effects have not been reported following ingestion of large doses of oral contraceptives by young children. Overdosage may cause nausea and withdrawal bleeding in females. In case of overdosage, contact your healthcare provider or pharmacist.

4. Other information

Your healthcare provider will take a medical and family history before prescribing oral contraceptives and will examine you. The physical examination may be delayed to another time if you request it and the healthcare provider believes that it is a good medical practice to postpone it. You should be reexamined at least once a year. Be sure to inform your healthcare provider if there is a family history of any of the conditions listed previously in this leaflet. Be sure to keep all appointments with your healthcare provider, because this is a time to determine if there are early signs of side effects of oral contraceptive use.

Do not use this drug for any condition other than the one for which it was prescribed. This drug has been prescribed specifically for you; do not give it to others who may want birth control pills.

HEALTH BENEFITS FROM ORAL CONTRACEPTIVES

In addition to preventing pregnancy, use of oral contraceptives may provide certain benefits. They are:

- Menstrual cycles may become more regular
- Blood flow during menstruation may be lighter and less iron may be lost. Therefore, anemia due to iron deficiency is less likely to occur
- Pain or other symptoms during menstruation may be encountered less frequently
- Ovarian cysts may occur less frequently
- Ectopic (tubal) pregnancy may occur less frequently
- Noncancerous cysts or lumps in the breast may occur less frequently
- Acute pelvic inflammatory disease may occur less frequently
- Oral contraceptive use may provide some protection against developing two forms of cancer: cancer of the ovaries and cancer of the lining of the uterus

If you want more information about birth control pills, ask your healthcare provider or pharmacist. They have a more technical leaflet called the Professional Labeling, which you may wish to read.

Manufactured by:
Warner Chilcott Company, LLC
Fajardo, PR 00738
Marketed by:
Warner Chilcott (US), LLC
Rockaway, NJ 07866
1-800-521-8813

To report SUSPECTED ADVERSE REACTIONS, contact Warner Chilcott at 1-800-521-8813 or FDA at 1-800-FDA-1088 or www.fda.gov/medwatch.

0530G035 Revised October 2009

PRINCIPAL DISPLAY PANEL

Loestrin® 24 Fe

(norethindrone acetate and ethinyl estradiol tablets, USP and ferrous fumarate tablets)
1 mg/20 mcg

28-DAY REGIMEN

Loestrin® 24 Fe provides 24 days of active therapy

Each pouch contains 1 blister card of 28 tablets.

PATIENT INSERTS are enclosed for your use when dispensing Loestrin® 24 Fe

Each white tablet contains norethindrone acetate, 1 mg;
ethinyl estradiol, 20 mcg; each brown tablet contains
ferrous fumarate 75 mg; each blister card contains
24 white tablets and 4 brown tablets.

Usual Dosage--One tablet daily for 28 days as directed
by the physician. See Package Insert for Full Prescribing Information.

This package is not child resistant.

Keep this and all drugs out of the reach of children.

Store at 25° C (77° F); excursions permitted to 15 - 30° C (59 - 86° F)
[see USP Controlled Room Temperature].
See bottom flap for lot number and expiration date.
Ferrous fumarate tablets are not USP for dissolution and assay.

To report SUSPECTED ADVERSE REACTIONS, contact Warner Chilcott at 1-800-521-8813 or FDA at 1-800-FDA-1088 or www.fda.gov/medwatch.